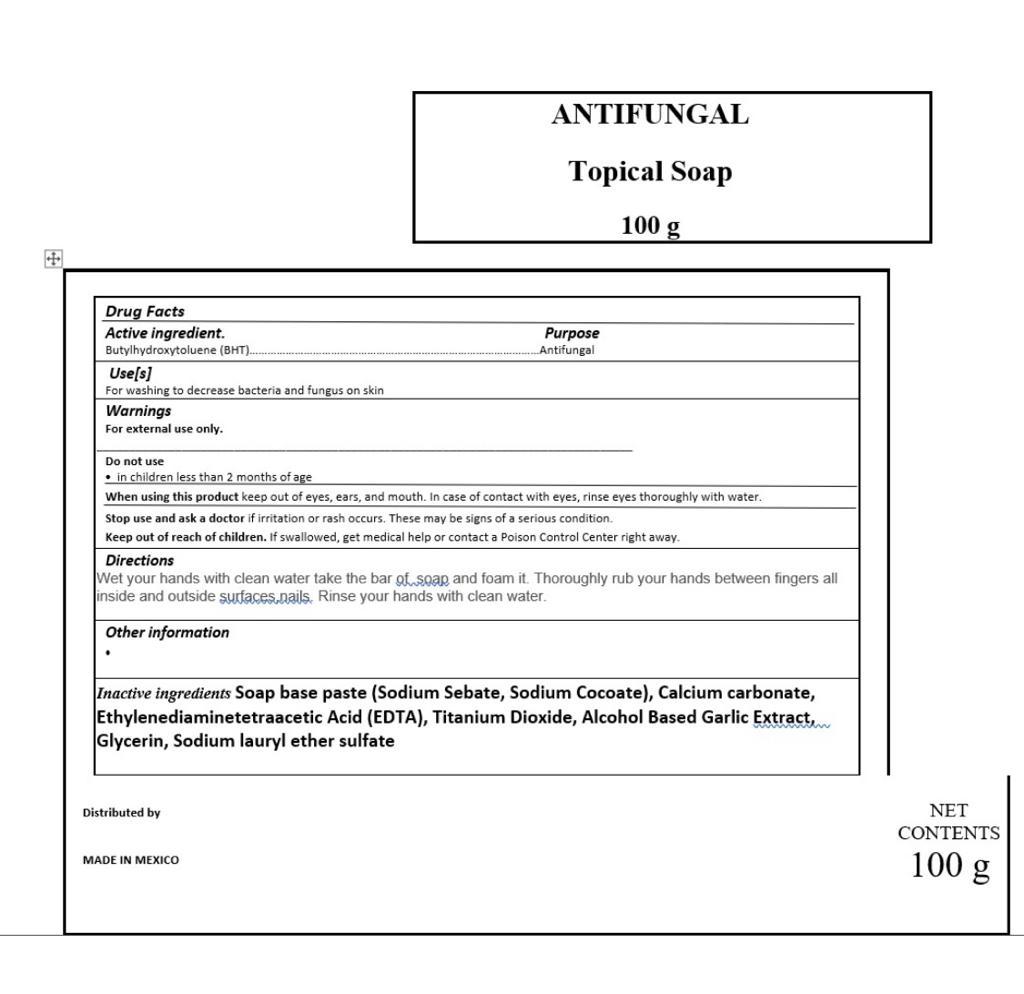 DRUG LABEL: ANTIFUNGAL
NDC: 79577-9000 | Form: SOAP
Manufacturer: PROMAQUILA DE COCULA, S.A. DE C.V.
Category: otc | Type: HUMAN OTC DRUG LABEL
Date: 20220623

ACTIVE INGREDIENTS: BUTYLATED HYDROXYTOLUENE 0.001 g/1 g; ALCOHOL 0.001 g/1 g
INACTIVE INGREDIENTS: EDETIC ACID 0.001 g/1 g; TITANIUM DIOXIDE 0.001 g/1 g; SODIUM LAURYL SULFATE 0.018 g/1 g; GLYCERIN 0.065 g/1 g; SODIUM BICARBONATE 0.8579 g/1 g; CALCIUM CARBONATE 0.046 g/1 g; GARLIC OIL 0.001 g/1 g

BULK ANTIFUNGAL SOAP

ACTIVE INGREDIENT SECTION

ACTIVE INGREDIENT Butylhydroxytoluene (BHT) .10 %

PURPOSE

PURPOSE ANTIFUNGAL

DOSAGE AND ADMINISTRATION

DIRECTIONS

Wet your hands with clean water take the bar of soap and foam it. Thoroughly rub your hands between fingers all inside and outside surfaces,nails. Rinse your hands with clean water.

WARNINGS

WARNING

FOR EXTERNAL USE ONLY

WARNINGS AND PRECAUTIONS

When using this product keep out of eyes, ears, and mouth. In case of contact with eyes, rinse eyes thoroughly with water.

KEEP OUT OF REACH OF CHILDREN

STOP USE SECTION

Stop use and ask a doctor if irritation or rash occurs. These may be signs of a serious condition.

USE

Use[s]

For washing to decrease bacteria and fungus on skin

INACTIVE INGREDIENTS

Soap base paste (Sodium Sebate, Sodium Cocoate)
Calcium carbonate
Ethylenediaminetetraacetic Acid
(EDTA)
Titanium Dioxide
Alcohol Based Garlic Extract, allium sativum l. bulb extract
Glycerin
Sodium lauryl ether sulfate

WARNING SECTION

For external use only.